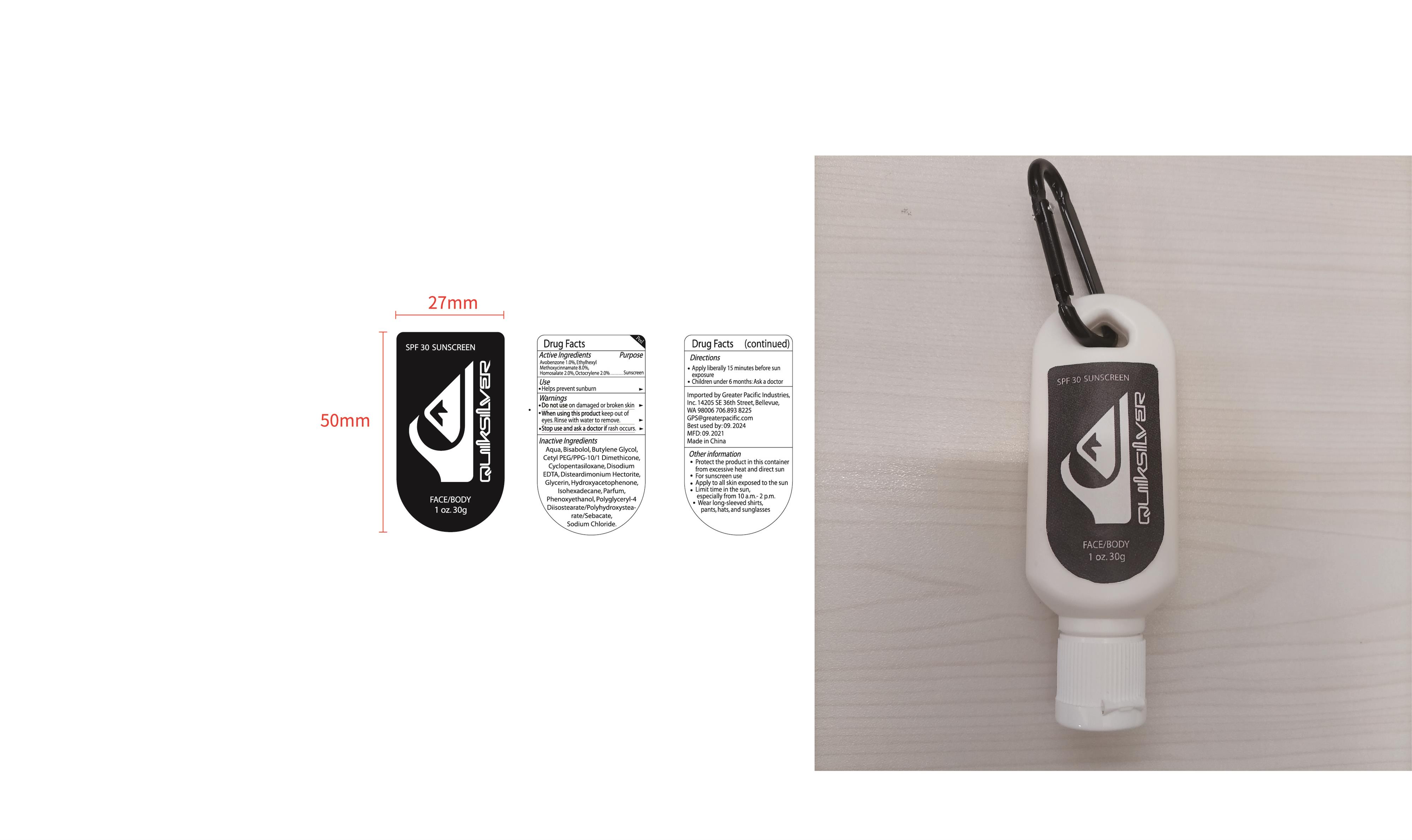 DRUG LABEL: QUIKSILVER SPF 30 SUNSCREEN
NDC: 54860-383 | Form: LOTION
Manufacturer: Shenzhen Lantern Scicence Co.,Ltd.
Category: otc | Type: HUMAN OTC DRUG LABEL
Date: 20210917

ACTIVE INGREDIENTS: HOMOSALATE 2 g/100 g; AVOBENZONE 1 g/100 g; OCTINOXATE 8 g/100 g; OCTOCRYLENE 2 g/100 g
INACTIVE INGREDIENTS: POLYGLYCERYL-4 ISOSTEARATE 1 g/100 g; PHENOXYETHANOL 0.4 g/100 g; DISTEARDIMONIUM HECTORITE 0.5 g/100 g; ROSA RUGOSA FLOWER 0.2 g/100 g; EDETATE DISODIUM ANHYDROUS 0.05 g/100 g; SODIUM CHLORIDE 1 g/100 g; HYDROXYACETOPHENONE 0.3 g/100 g; LEVOMENOL 0.1 g/100 g; DIMETHICONE CROSSPOLYMER (450000 MPA.S AT 12% IN CYCLOPENTASILOXANE) 12 g/100 g; ISOHEXADECANE 8 g/100 g; CETYL PEG/PPG-10/1 DIMETHICONE (HLB 5) 2 g/100 g; BUTYLENE GLYCOL 3 g/100 g; WATER 53.45 g/100 g; GLYCERIN 5 g/100 g

QUIKSILVER SPF 30 SUNSCREEN

Active Ingredient

Active Ingredient Purpose

Avobenzone 1.0%

Ethylhexyl Methoxycinnamate 8.0%

Homosalate 2.0%

Octocrylene 2.0% ..........................................Sunscreen

Inactive ingredients

AQUA,CYCLOPENTASILOXANE,ISOHEXADECANE,ETHYLHEXYL METHOXYCINNAMATE,GLYCERIN,BUTYLENE GLYCOL,CETYL PEG/PPG-10/1 DIMETHICONE,HOMOSALATE,OCTOCRYLENE,SODIUM CHLORIDE,AVOBENZONE,POLYGLYCERYL-4 DIISOSTEARATE/POLYHYDROXYSTEARATE/SEBACATE,DISTEARDIMONIUM HECTORITE,PHENOXYETHANOL,HYDROXYACETOPHENONE,PARFUM,BISABOLOL,DISODIUM EDTA.

Directions

Apply liberaaly 15 minutes before sun exposure.

Children under 6 months; Ask a doctor.

When using this product

keep out of eyes. In case of contact with eyes, flush thoroughly with water.

Do not inhale or ingest.

Avoid contact with broken skin.

Other information

Do not store above 105F.

May discolor some fabrics.

Harmful to wood finishes and plastics.

When using this product

Keep out of eyes,Rinse with water to remove.

Purpose

Sunscreen

Stop use and ask a doctor

if rash occurs.

Do not use

on danaged or broken skin.

Other information

Protect the product in this container from excessive heat and direct sun.

For sunscreen use

Apply to all skin exposed to the sun

Limit time in the sun,especially from 10 a.m.-2 p.m.

Wear long-s;eeved shirts,pants,hats,and sunglasses.